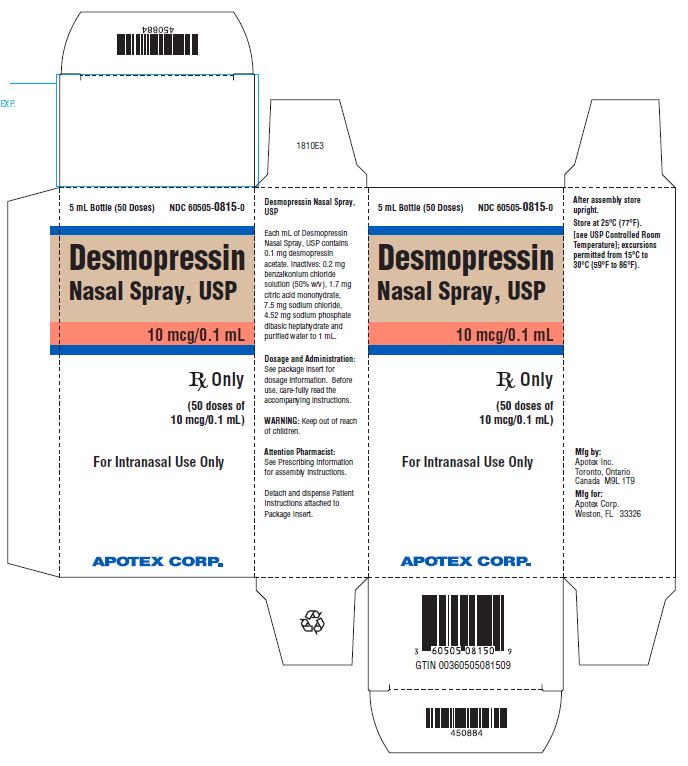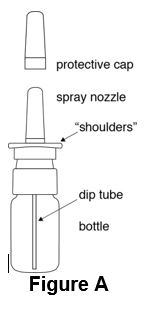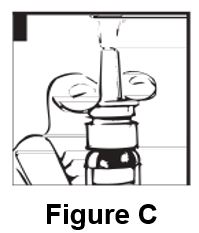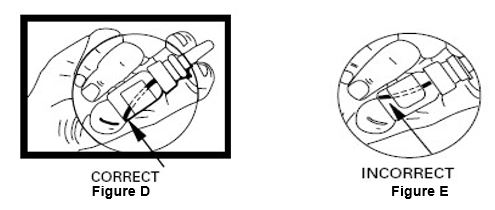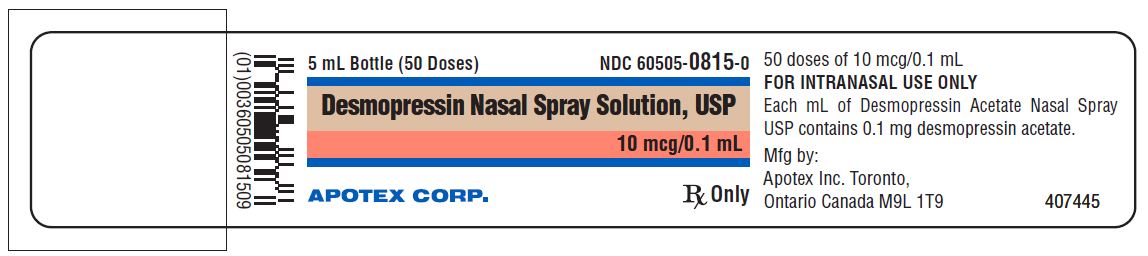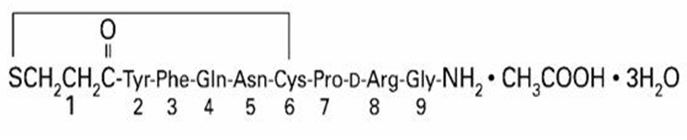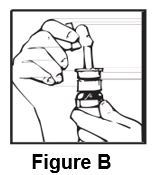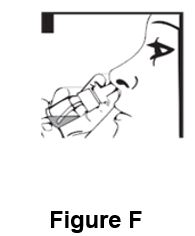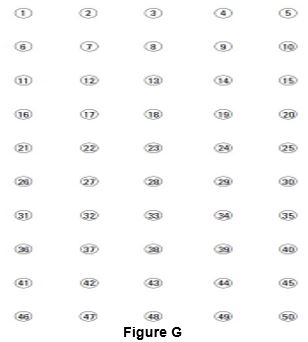 DRUG LABEL: DESMOPRESSIN ACETATE
NDC: 60505-0815 | Form: SPRAY
Manufacturer: Apotex Corp.
Category: prescription | Type: HUMAN PRESCRIPTION DRUG LABEL
Date: 20250822

ACTIVE INGREDIENTS: DESMOPRESSIN ACETATE 10 ug/1 1
INACTIVE INGREDIENTS: SODIUM CHLORIDE; CITRIC ACID MONOHYDRATE; SODIUM PHOSPHATE, DIBASIC, HEPTAHYDRATE; BENZALKONIUM CHLORIDE; WATER 

HIGHLIGHTS OF PRESCRIBING INFORMATION

These highlights do not include all the information needed to use DESMOPRESSIN NASAL SPRAY safely and effectively. See full prescribing information for DESMOPRESSIN NASAL SPRAY.
DESMOPRESSIN nasal spray
Initial U.S. Approval: 1978

1 INDICATIONS AND USAGE

Desmopressin nasal spray is a vasopressin analog indicated as antidiuretic replacement therapy in the management of central diabetes insipidus for adults and pediatric patients 4 years of age and older (1)

Limitations of Use:

Desmopressin nasal spray is not indicated for:

- Treatment of nephrogenic diabetes insipidus (1)
- Treatment of primary nocturnal enuresis (1, 5.1)
- Use in patients with conditions that compromise intranasal route of administration (1, 5.2)
- Use in patients with an impaired level of consciousness (1)
- Use in patients requiring doses less than 10 mcg or doses that are not multiples of 10 mcg (1,3)

2 DOSAGE AND ADMINISTRATION

- For intranasal use only (2.1)
- Instruct patients to prime pump prior to use (2.1)
- Adults: 10 mcg to 40 mcg daily (either as a single dose or divided into two or three daily doses) (2.2)
- Pediatrics: 10 mcg once daily into one nostril up to 30 mcg once daily (or 30 mcg divided as 20 mcg during the morning and 10 mcg at night) (2.2)
- See the Full Prescribing Information for recommendations for switching between desmopressin acetate formulations (2.3)

3 DOSAGE FORMS AND STRENGTHS

Nasal Spray: 10 mcg per 0.1 mL spray, available in a 5 mL bottle with spray pump delivering 50 sprays (3)

4 CONTRAINDICATIONS

- Known hypersensitivity to desmopressin acetate or to any of the components of desmopressin nasal spray (4, 6)
- Patients with renal impairment (creatinine clearance below 50 mL/min) (4, 8.6, 12.3)
- Hyponatremia or a history of hyponatremia (4, 5.1)

5 WARNINGS AND PRECAUTIONS

- Hyponatremia: Instruct patients about proper fluid restriction and monitor serum sodium as needed (2.1, 5.1)
- Altered Absorption in Patients with Nasal Mucosa Abnormalities: May occur with chronic administration, and require use of other formulations instead (5.2)

6 ADVERSE REACTIONS

Adverse reactions that have been identified in patients administered desmopressin nasal spray are headache, nasal congestion, rhinitis, nosebleed, sore throat, cough, upper respiratory infections, nausea, flushing, and mild abdominal cramps (6)

To report SUSPECTED ADVERSE REACTIONS, contact Apotex Corp. at 1-800-706-5575 or FDA at 1-800-FDA-1088 or www.fda.gov/medwatch

7 DRUG INTERACTIONS

- Drugs that Increase Risk of Hyponatremia: Requires more frequent monitoring of serum sodium (7.1)
- Other Vasoconstrictors: Concomitant use may elevate blood pressure and require a reduction in desmopressin nasal spray dosage (7.2)

8 USE IN SPECIFIC POPULATIONS

- Pediatric Use: Use requires careful fluid intake restriction to prevent hyponatremia with water intoxication (5.1, 8.4)
- Geriatric Use: Carefully monitor renal function; restrict fluid intake to prevent hyponatremia with water intoxication (5.1, 8.5)

FULL PRESCRIBING INFORMATION

1 INDICATIONS AND USAGE

Desmopressin nasal spray is indicated as antidiuretic replacement therapy in the management of central diabetes insipidus in adults and pediatric patients 4 years of age and older

Limitations of Use:

Desmopressin nasal spray is not indicated for:

- Treatment of nephrogenic diabetes insipidus,
- Treatment of primary nocturnal enuresis [see Warnings and Precautions (5.1)],
- Use in patients with conditions that compromise the intranasal route of administration (e.g., severe nasal congestion and blockage, nasal mucosa atrophy, severe atrophic rhinitis, recent nasal surgery such as transsphenoidal hypophysectomy) [see Warnings and Precautions (5.2)].
- Use in patients with an impaired level of consciousness,
- Use in patients requiring doses less than 10 mcg or doses that are not multiples of 10 mcg [see Dosage Forms and Strengths (3)].

2 DOSAGE AND ADMINISTRATION

2.1 Important Administration Instructions

Administer desmopressin nasal spray by intranasal use only. Instruct patients about appropriate fluid restriction during desmopressin nasal spray treatment [see Warnings and Precautions (5.1)].

Must prime the spray pump prior to the first use. Instruct patients to:

- Prime pump by pressing down on pump four times (if the spray pump is not used for one week, re-prime the pump by pressing down on the pump once).
- Discard desmopressin nasal spray after 50 sprays since the amount delivered thereafter may be substantially less than the recommended dosage.

2.2 Recommended Dosage

The use of desmopressin nasal spray is not indicated for patients who require less than 10 mcg doses or doses that are not multiples of 10 mcg because the spray pump can only deliver doses of 10 mcg [see Indications and Usage (1)]. If other doses are required, use another desmopressin acetate product.

Individualize the dosage of desmopressin nasal spray for each patient with particular attention in pediatric and elderly patients and adjust according to the diurnal pattern of response to limit nocturia and to ensure fluid intake with respect to urine output is not excessive [see Warnings and Precautions (5.1)]. Monitor continued response to desmopressin nasal spray by urine volume and osmolality to ensure adequate diuresis to limit the risk of hyponatremia, and include measurements of serum sodium and plasma osmolality as needed.

Adults

The recommended dosage in adults is 10 mcg once daily into one nostril up to 40 mcg once daily (or 40 mcg divided into two or three daily doses). If administered more than once a day, adjust for an adequate diurnal rhythm of urine output.

Pediatric Patients

- For pediatric patients requiring doses less than 10 mcg, desmopressin nasal spray is not indicated.
- For pediatric patients 4 years of age and older, the recommended starting dosage of desmopressin nasal spray is 10 mcg once daily into one nostril. The dose can be titrated up to 30 mcg once daily (or 30 mcg divided into two daily doses, typically with 20 mcg given in the morning and 10 mcg given at nighttime). If administered more than once a day, adjust for an adequate diurnal rhythm of urine output.

Because administration of desmopressin acetate can be associated with decreased responsiveness with prolonged use, consider increasing the dosage of desmopressin nasal spray if patients demonstrate decreased response over a long period of time.

2.3 Switching Between Desmopressin Acetate Formulations

When switching from the desmopressin acetate injection to desmopressin nasal spray, administer 10 times the amount of desmopressin acetate, rounding down to the nearest 10 mcg. When switching from the desmopressin acetate tablets to desmopressin nasal spray individual dose titration is required because intranasal desmopressin is approximately 10 to 40 fold more potent than oral (tablet) desmopressin.

3 DOSAGE FORMS AND STRENGTHS

Desmopressin nasal spray pump delivers 10 mcg (0.1 mL) of desmopressin acetate per spray. Desmopressin nasal spray is available as a 5 mL bottle with spray pump delivering 50 sprays.

4 CONTRAINDICATIONS

Desmopressin nasal spray is contraindicated in patients with:

- Known hypersensitivity to desmopressin acetate or to any of the components of desmopressin nasal spray. Severe allergic reactions and anaphylaxis have been reported [see Adverse Reactions (6)].
- Renal impairment defined as estimated creatinine clearance (CLcr) by Cockcroft-Gault equation less than 50 mL/min [see Use in Specific Populations (8.6) and Clinical Pharmacology (12.3)].
- Hyponatremia or a history of hyponatremia [see Warnings and Precautions (5.1)].

5 WARNINGS AND PRECAUTIONS

5.1 Hyponatremia

Excessive fluid intake when urine output is limited by the antidiuretic effect of desmopressin may lead to water intoxication with hyponatremia. Cases of hyponatremia have been reported from postmarketing experience in patients treated with desmopressin acetate. Unless properly diagnosed and treated, hyponatremia can be fatal.

All patients receiving desmopressin nasal spray should be observed for the following signs or symptoms associated with hyponatremia: headache, nausea/vomiting, decreased serum sodium, weight gain, restlessness, fatigue, lethargy, disorientation, depressed reflexes, loss appetite, irritability, muscle weakness, muscle spasms or cramps and abnormal mental status such as hallucinations, decreased consciousness, and confusion. Severe symptoms due to an extreme decrease in serum sodium and plasma osmolality may include one or a combination of the following: seizure, coma, and/or respiratory arrest.

In order to decrease the risk of water intoxication with hyponatremia, fluid restriction is recommended. Careful fluid intake restriction is particularly important in pediatric and geriatric patients because these patients are at greater risk of developing hyponatremia [see Use in Specific Populations (8.4, 8.5)]. More frequent monitoring of serum sodium levels is recommended in the following patients: those with conditions associated with fluid and electrolyte imbalance, such as cystic fibrosis, heart failure, renal disorders, habitual or psychogenic polydipsia or those taking concomitant drugs that may cause hyponatremia [see Drug Interactions (7.1)].

Desmopressin nasal spray is not an indicated formulation for the treatment of primary nocturnal enuresis due to a higher risk of hyponatremia and hyponatremic convulsions with the use of the nasal spray formulation compared to desmopressin tablets seen in postmarketing reports [see Indications and Usage (1)].

5.2 Altered Absorption in Patients With Nasal Mucosa Abnormalities

Chronic administration of desmopressin nasal spray may result in changes to nasal mucosa. Nasal mucosa abnormalities (such as scarring and edema) due to chronic administration, or due to other causes (nasal blockage, nasal mucosal atrophy, severe atrophic rhinitis, recent nasal surgery such as transsphenoidal hypophysectomy) may cause erratic, unreliable absorption. Avoid use of desmopressin nasal spray in such patients [see Indications and Usage (1)] and consider use of other formulations of desmopressin acetate given by other routes of administration.

6 ADVERSE REACTIONS

The following serious reactions are described below and elsewhere in the labeling:

- Hyponatremia [see Warnings and Precautions (5.1)].
- Altered Absorption in Patients with Changes in Nasal Mucosa [see Warnings and Precautions (5.2)].

The following adverse reactions have been identified during post-approval use of desmopressin acetate. Because these reactions are reported voluntarily from a population of uncertain size, it is not always possible to reliably estimate their frequency or establish a causal relationship to drug exposure:

Increase in blood pressure, headache, nasal congestion, rhinitis, nosebleed, sore throat, cough, upper respiratory infections, nausea, flushing, and abdominal cramps.

Water intoxication with hyponatremia

Hyponatremic convulsions associated with concomitant use of the following medications: oxybutinin and imipramine [see Drug Interactions (7.1)].

Severe allergic reactions and anaphylaxis [see Contraindications (4)]

7 DRUG INTERACTIONS

7.1 Other Drugs that may Increase Risk of Hyponatremia

The concomitant administration of desmopressin nasal spray with other drugs that may increase the risk of water intoxication with hyponatremia, (e.g., tricyclic antidepressants, selective serotonin re-uptake inhibitors, chlorpromazine, opiate analgesics, NSAIDs, lamotrigine, oxybutynin and carbamazepine) requires more frequent serum sodium monitoring [see Warnings and Precautions (5.1) and Adverse Reactions (6)].

7.2 Other Vasoconstrictors

Desmopressin acetate can elevate blood pressure. Use of large doses of desmopressin nasal spray with other vasoconstrictors may require a reduction of the desmopressin dosage [see Adverse Reactions (6)].

8 USE IN SPECIFIC POPULATIONS

8.1 Pregnancy

Risk summary

Prolonged experience with desmopressin in pregnant women over several decades, based on the available published data and case reports, did not identify a drug associated risk of major birth defects, miscarriage or adverse maternal or fetal outcomes. In addition, in vitro studies with human placenta demonstrate poor placental transfer of desmopressin. No adverse developmental outcomes were observed in animal reproduction studies with administration of desmopressin during organogenesis to pregnant rats and rabbits at doses approximately <1 and 38 times, respectively, the maximum recommended human dose based on body surface area (mg/m^2) (see Data).

The estimated background risk of major birth defects and miscarriage for the indicated population are unknown. In the US general population, the estimated background risk of major birth defects and miscarriage in clinically recognized pregnancies is 2 to 4% and 15 to 20%, respectively.

Data

Animal Data Desmopressin acetate at up to 50 ng/kg/day was given by subcutaneous injection to pregnant rats, from gestation day 1 to 20 during the period of early embryonic development and organogenesis without teratogenic effects. Desmopressin acetate at up to 10 mcg/kg/day was given to pregnant rabbits by subcutaneous injection from gestation day 6 to 18 during fetal organogenesis without teratogenic effects. These doses of desmopressin acetate represent approximately <1 times (rat) and 38 times (rabbit) the maximum recommended human dose based on body surface area (mg/m^2).

8.2 Lactation

Risk Summary

Breastfeeding is not expected to result in clinically relevant exposure of the infant to desmopressin following maternal intranasal administration. Desmopressin is poorly transferred into human breastmilk at negligible amounts (see Data). There is no information on the effects of desmopressin on the breastfed infant or on milk production. The developmental and health benefits of breastfeeding should be considered along with the mother’s clinical need for desmopressin nasal spray and any potential adverse effects on the breastfed infant from desmopressin nasal spray or from the underlying maternal condition.

Data

A trial was conducted in six healthy lactating women, at greater than 4 months postpartum, to evaluate intranasal administration of 300 mcg single dose of another desmopressin product (7.5 times the recommended adult dose of desmopressin nasal spray). Samples of maternal plasma and breastmilk were obtained at 0, 30, 60, 120, 240, 360 and 480 min after the drug administration. At 8 hours after dose intake, the levels in the milk ranged between 4.16 and 101 pg/ml, and the plasma levels ranged between 40 and 242 pg/ml. The total amount of desmopressin present in the milk over the 8 hours ranged between 491 pg and 16 ng, which corresponds to 0.0001 to 0.005% of the administered dose to the breastfeeding mother.

8.4 Pediatric Use

Desmopressin nasal spray is indicated as antidiuretic replacement therapy in the management of central diabetes insipidus in pediatric patients 4 years of age and older. Desmopressin nasal spray is not indicated in pediatric patients less than 4 years of age.

Use of desmopressin nasal spray in pediatric patients 4 years of age and older is supported by evidence from adults and pediatric patients with central diabetes insipidus. Use in pediatric patients requires careful fluid intake restriction to prevent possible water intoxication with hyponatremia [see Warnings and Precautions (5.1)].

8.5 Geriatric Use

Clinical studies of desmopressin nasal spray did not include sufficient numbers of subjects aged 65 and over to determine whether they respond differently from younger subjects. In general, dose selection for an elderly patient should be cautious, usually starting at a low end of the dosing range, reflecting the greater frequency of decreased hepatic, renal, or cardiac function, and of concomitant disease or drug therapy.

Because elderly patients are more likely to have renal impairment, care should be taken in dose selection, and monitoring renal function is recommended [see Contraindications (4), Use in Specific Populations (8.6)].

Use of desmopressin nasal spray in geriatric patients requires careful fluid intake restriction to prevent possible water intoxication with hyponatremia [see Warnings and Precautions (5.1)].

8.6 Renal Impairment

Desmopressin acetate is substantially excreted by the kidney, and the risk of adverse reactions may be greater in patients with renal impairment than patients with normal renal function. Desmopressin nasal spray is contraindicated in patients with estimated CLcr by Cockcroft-Gault equation less than 50 mL/min [see Clinical Pharmacology (12.1, 12.3), Contraindications (4)].

10 OVERDOSAGE

Signs of desmopressin acetate overdosage may include confusion, drowsiness, continuing headache, problems with passing urine, and rapid weight gain due to fluid retention [see Warnings and Precautions (5.1)]. In case of overdosage, reduce the dosage, decrease the frequency of administration, or discontinue desmopressin nasal spray. There is no known specific antidote for desmopressin acetate.

11 DESCRIPTION

Desmopressin nasal spray, USP is a synthetic analogue of the natural pituitary hormone 8-arginine vasopressin (ADH), an antidiuretic hormone affecting renal water conservation. The structural formula for the active ingredient is:

Mol. wt. 1183.34 g/mol

Molecular formula: C46H64N14O12S2 • C2H4O2 • 3H2O

Chemical name: 1-(3-mercaptopropionic acid)-8-D-arginine vasopressin monoacetate (salt) trihydrate.

Desmopressin nasal spray, USP is provided as an aqueous solution for intranasal use.

Each mL contains:

Desmopressin acetate 0.1 mg

Inactive:

Benzalkonium chloride solution (50% w/v) 0.2 mg

Citric acid monohydrate 1.7 mg

Sodium chloride 7.5 mg

Sodium phosphate dibasic heptahydrate 4.52 mg

Purified water to 1 mL

The desmopressin nasal spray, USP compression pump delivers 0.1 mL (10 mcg) of desmopressin acetate per spray.

12 CLINICAL PHARMACOLOGY

12.1 Mechanism of Action

The antidiuretic effects of desmopressin are mediated by stimulation of vasopressin 2 (V2) receptors, thereby increasing water re-absorption in the kidney, and hence reducing urine production. Desmopressin is a replacement hormone for antidiuretic hormone in the treatment of central diabetes insipidus. The change in structure of arginine vasopressin to desmopressin acetate resulted in a decreased vasopressor action and decreased actions on visceral smooth muscle relative to the enhanced antidiuretic activity, so that clinically effective antidiuretic doses were usually below threshold levels for effects on vascular or visceral smooth muscle.

12.2 Pharmacodynamics

The use of desmopressin nasal spray in patients with central diabetes insipidus reduces urinary output, increases urine osmolality, and decreases plasma osmolality.

12.3 Pharmacokinetics

Absorption: Desmopressin acetate is absorbed through the nasal mucosa.

Elimination: Desmopressin acetate exhibits a biphasic elimination profile, with half-lives of 7.8 and 75.5 minutes for the initial and terminal phases, respectively.

Specific Populations

Renal Impairment: Desmopressin acetate is mainly excreted in the urine. A pharmacokinetic study was conducted in subjects with normal renal function and patients with mild, moderate, and severe renal impairment (n=24, 6 subjects each group) with a single 2 mcg dose of desmopressin acetate injection (this results in approximately 20 times the exposure of 10 mcg of desmopressin nasal spray). The terminal half-life was 2.8 hours in subjects with normal renal function, 4.0 hours in mild renal impairment, 6.6 hours in moderate renal impairment and 8.7 hours in severe renal impairment. In patients with mild, moderate and severe renal impairment, mean desmopressin exposure was 1.5 fold, 2.4 fold and 3.6 fold higher, respectively compared to that of subjects with normal renal function [see Contraindications (4), Use in Specific Populations (8.6)].

13 NONCLINICAL TOXICOLOGY

13.1 Carcinogenesis, Mutagenesis, Impairment of Fertility

Studies with desmopressin acetate have not been performed to evaluate carcinogenic potential, mutagenic potential, or effects on fertility.

16 HOW SUPPLIED/STORAGE AND HANDLING

16.1 How Supplied

Desmopressin nasal spray, USP is available in a 5 mL bottle with a nasal spray pump dispenser with dust cover and patient instruction sheet delivering 50 sprays of 10 mcg (NDC 60505-0815-0).

16.2 Storage and Handling

Store at 25°C (77°F) [see USP Controlled Room Temperature]; excursions permitted from 15°C to 30°C (59°F to 86°F).
AFTER ASSEMBLY, STORE UPRIGHT.

Keep out of the reach of children.

17 PATIENT COUNSELING INFORMATION

Advise the patient to read the FDA-approved patient labeling (Patient Information and Instructions for Use)

Administration

- Inform caregivers for pediatric patients that administration should be supervised to ensure the patient receives the prescribed dose.
- Inform patients that the pump must be primed prior to first use and again if not used for greater than one week. Inform patients that the desmopressin nasal spray bottle delivers 50 sprays of 10 mcg each following the initial 4 priming pumps.
- Inform patients to discard any solution remaining after 50 sprays since the amount delivered thereafter may be substantially less than 10 mcg of drug.
  Monitoring

- Educate patients about the signs and symptoms of hyponatremia and advise them to contact a healthcare provider if such symptoms occur.
- Discuss downward adjustment of fluid intake and monitoring of urine output with patients.

APOTEX INC.

Desmopressin Nasal Spray, USP

10 mcg/ 0.1 mL

Manufactured by
Apotex Inc. Toronto,
Ontario Canada M9L 1T9

Manufactured for
Apotex Corp. Weston,

Florida 33326

September 2022

Patient Information

Desmopressin Nasal Spray, USP 10 mcg per 0.1 mL

(des·mo·pres·sin)

For Intranasal Use Only

What is desmopressin nasal spray?

Desmopressin nasal spray is a prescription medicine called a vasopressin analog used as an antidiuretic replacement to manage central diabetes insipidus.

- Desmopressin nasal spray is not effective in the treatment of nephrogenic diabetes insipidus.
- Desmopressin nasal spray should not be used in people with nasal problems that may keep them from using a nasal spray.

Who should not use desmopressin nasal spray?

Do not use desmopressin nasal spray if you:

- are allergic to desmopressin or any of the ingredients in desmopressin nasal spray. Some people have had severe allergic reactions while taking desmopressin nasal spray. See the end of this Patient Information for a complete list of ingredients in desmopressin nasal spray.
- have kidney problems
- have or have had low levels of sodium in your blood (hyponatremia)

What should I tell my healthcare provider before using desmopressin nasal spray? Before using desmopressin nasal spray, tell your healthcare provider about all your medical conditions including if you:

- have or have had nasal sores, nasal surgery, nasal injury, or have problems such as a stuffy nose or trouble breathing through your nose.
- have or have had any heart, blood circulation, or blood pressure problems
- have a condition that causes fluid or water imbalance problems such as cystic fibrosis, or heart failure.
- have or have had a condition that causes you to be very thirsty
- are pregnant or plan to become pregnant. It is not known if desmopressin will harm your unborn baby.
- are breastfeeding or plan to breastfeed. It is not known if desmopressin passes into your breast milk. You and your healthcare provider should decide if you will use desmopressin nasal spray.

Tell your healthcare provider about all the medicines you take, including prescription and over-the-counter medicines, vitamins, and herbal supplements.

How should I use desmopressin nasal spray?

- Read the Instructions for Use that comes with your desmopressin nasal spray.
- Use desmopressin nasal spray exactly as your healthcare provider tells you to use it.
- Your healthcare provider may change your dose of desmopressin nasal spray if needed.

What are the possible side effects of desmopressin nasal spray?

Desmopressin nasal spray may cause serious side effects including:

- low levels of sodium in the blood (hyponatremia). People using desmopressin nasal spray are at risk for low sodium levels in the blood, water intoxication, and fluid overload. Follow your healthcare provider’s instructions on limiting the amount of fluid you can drink when using desmopressin nasal spray.
- Do not drink more than you need to satisfy your thirst. You can have serious side effects such as seizures, coma, and death from drinking too much fluid.
- Children and the elderly are at higher risk for these problems and should follow their healthcare provider’s limits on drinking fluids.
- Call your healthcare provider right away if you have any of the following symptoms while using desmopressin nasal spray. They may mean that your blood sodium level is too low.
- headache
- nausea, vomiting
- weight gain
- restlessness
- tiredness
- sleepiness
- disorientation
- loss of appetite
- feeling irritable
- feeling weak
- muscle cramps
- hallucinations
- confusion
- nasal scarring or swelling. Some people using desmopressin nasal spray for long periods of time may have nasal problems such as scarring or swelling. This may affect how well desmopressin nasal spray works for you. The most common side effects of desmopressin nasal spray include: headache, stuffy nose, runny nose, nosebleed, sore throat, cough, upper respiratory infections, nausea, flushing, and stomach cramps. Call your doctor for medical advice about side effects. You may report side effects to FDA at 1-800-FDA-1088.

General information about the safe and effective use of desmopressin nasal spray. Medicines are sometimes prescribed for purposes other than those listed in a Patient Information leaflet. Do not use desmopressin nasal spray for a condition for which it was not prescribed. Do not give desmopressin nasal spray to other people, even if they have the same symptoms that you have. It may harm them. You can ask your healthcare provider or pharmacist for information about desmopressin nasal spray that is written for health professionals. For more information call Apotex Corp. at 1-800-706-5575.

What are the ingredients in desmopressin nasal spray?

Active ingredient: desmopressin acetate

Inactive ingredients: benzalkonium chloride solution (50% w/v), citric acid monohydrate, sodium chloride, sodium phosphate dibasic heptahydrate, and purified water

This Patient Information has been approved by the Food and Drug Administration

APOTEX INC.

Desmopressin Nasal Spray, USP 10 mcg/ 0.1 mL

Manufactured by
Apotex Inc. Toronto,
Ontario Canada M9L 1T9

Manufactured for
Apotex Corp.
Weston, Florida
33326

September 2022

Instructions for Use

Desmopressin Nasal Spray, USP 10 mcg per 0.1 mL

For Intranasal Use Only

Read these instructions before using desmopressin nasal spray, and each time you get a refill. There may be new information. This information does not take the place of talking to your healthcare provider about your medical condition or treatment.

Instruction For Assembly of Spray Pump

Assemble desmopressin nasal spray, USP, 0.01% prior to dispensing to the patient, according to the following instructions:

1. Open the carton and remove the spray pump and solution bottle.

2. Assemble the desmopressin nasal spray solution by unscrewing the white cap from the solution bottle and screwing the spray pump tightly onto the bottle. Make sure the protective cap is on the spray pump.

3. Return desmopressin nasal spray solution bottle to the carton for dispensing to the patient.

Children should be helped by an adult when using desmopressin nasal spray, to make sure the right amount of medicine is used.

The parts of your desmopressin nasal spray pump (see Figure A):

Priming your desmopressin nasal spray:

Your desmopressin nasal spray pump must be primed before you use it for the first time.

- Remove the protective cap (see Figure B).

- Press down on the shoulders at the top of your desmopressin nasal spray pump 4 times. Hold the spray tip away from your face and eyes (see Figure C).

- After your desmopressin nasal spray pump is primed, it will spray 10 micrograms (1 dose) of medicine each time it is pressed.

Using your desmopressin nasal spray:

Step 1. Remove the protective cap.

Step 2. To make sure you get the right dose of medicine tilt your desmopressin nasal spray pump so the dip tube inside the bottle draws the medicine up from the deepest part of the medicine inside the bottle (see Figures D and E).

Step 3. Put the spray nozzle tip of your desmopressin nasal spray into your nostril and press the spray pump 1 time for 1 dose. (see Figure F). If 2 doses are prescribed, spray each nostril 1 time.

Step 4. Put the protective cap back on the spray nozzle tip when you finish using your desmopressin nasal spray.

Keeping track of your Nasal Sprays:

- Use the check-off chart to help you keep track of your desmopressin nasal sprays used (see Figure G).

Desmopressin Nasal Spray

50-Spray Check-off Chart

- Keep this chart with your desmopressin nasal spray or put it someplace where you can easily get it.
- Check off number 1 on the chart with your first dose of desmopressin nasal spray. Check off the numbers after each use of your desmopressin nasal spray. If your healthcare provider prescribed a 2-spray dose, then 2 numbers should be checked off.
- Your desmopressin nasal spray holds 50 sprays with the right amount of medicine in each spray.
- If any medicine is left in your desmopressin nasal spray after 50 sprays, do not use it. You may not get the right amount of medicine.
- Throw away your desmopressin nasal spray after 50 sprays.
- Do not count the priming sprays. Your desmopressin nasal spray has been filled with extra medicine for your priming sprays.
- Do not try to remove any medicine from your desmopressin nasal spray pump and place it in another bottle.

How should I store desmopressin nasal spray?

Store at 25°C (77°F) [see USP Controlled Room Temperature]; excursions permitted from 15°C to 30°C (59°F to 86°F).AFTER ASSEMBLY, STORE UPRIGHT.

Keep out of the reach of children.

This Instructions for Use has been approved by the U.S. Food and Drug Administration.

APOTEX INC.

Desmopressin Nasal Spray, USP 10 mcg/ 0.1 mL

Manufactured by
Apotex Inc. Toronto,
Ontario Canada M9L 1T9

Manufactured for
Apotex Corp. Weston,
Florida 33326

September 2022

PRINCIPAL DISPLAY PANEL - 5 mL Carton Label

APOTEX CORP. NDC 60505-0815-0

Desmopressin Nasal Spray Solution USP, 0.01%

Rx Only

5 mL

PRINCIPAL DISPLAY PANEL - 5 mL Bottle Label

APOTEX CORP. NDC 60505-0815-0

Desmopressin Nasal Spray Solution USP, 0.01%

Rx Only

5 mL